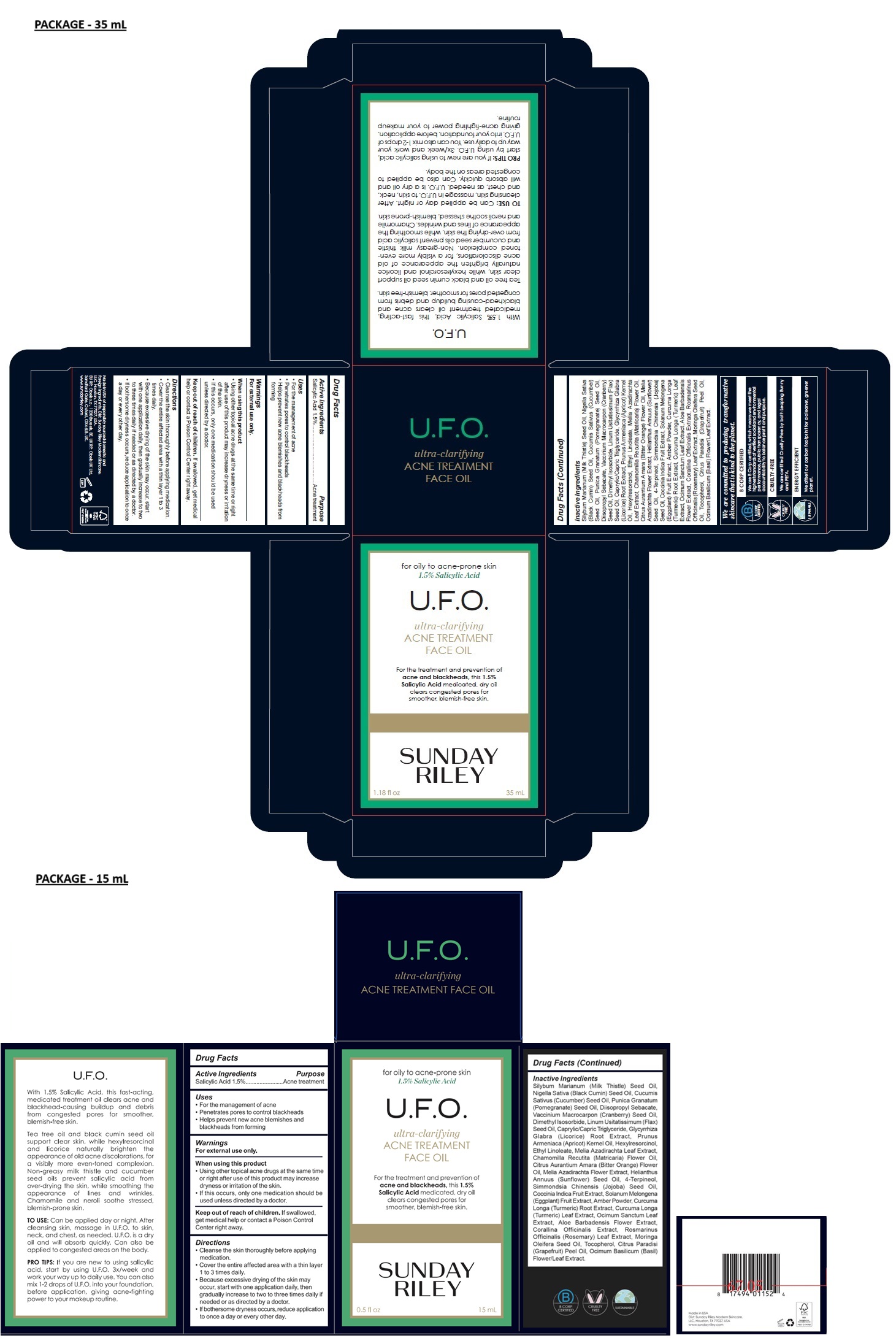 DRUG LABEL: SUNDAY RILEY U.F.O Acne Treatment Face Oil
NDC: 73001-460 | Form: OIL
Manufacturer: Sunday Riley Modern Skincare, LLC
Category: otc | Type: HUMAN OTC DRUG LABEL
Date: 20250114

ACTIVE INGREDIENTS: SALICYLIC ACID 15 mg/1 mL
INACTIVE INGREDIENTS: SILYBUM MARIANUM SEED OIL; NIGELLA SATIVA SEED OIL; CUCUMBER SEED OIL; POMEGRANATE SEED OIL; DIISOPROPYL SEBACATE; CRANBERRY SEED OIL; DIMETHYL ISOSORBIDE; LINSEED OIL; MEDIUM-CHAIN TRIGLYCERIDES; GLYCYRRHIZA GLABRA; APRICOT KERNEL OIL; HEXYLRESORCINOL; ETHYL LINOLEATE; AZADIRACHTA INDICA LEAF; CHAMOMILE FLOWER OIL; CITRUS AURANTIUM FLOWER OIL; AZADIRACHTA INDICA FLOWER; SUNFLOWER OIL; 4-TERPINEOL, (+/-)-; JOJOBA OIL; COCCINIA GRANDIS FRUIT; EGGPLANT; AMBER; TURMERIC; CURCUMA LONGA LEAF; HOLY BASIL LEAF; ALOE VERA FLOWER; CORALLINA OFFICINALIS; ROSEMARY; MORINGA OLEIFERA SEED OIL; TOCOPHEROL; GRAPEFRUIT OIL; OCIMUM BASILICUM FLOWERING TOP

SUNDAY RILEY U.F.O. ACNE TREATMENT FACE OIL

Active Ingredients

Salicylic Acid 1.5%

Purpose

Acne treatment

Uses

• For the management of acne

• Penetrates pores to control blackheads

• Helps prevent new acne blemishes and blackheads from forming

Warnings

For external use only.

When using this product

• Using other topical acne drugs at the same time or right after use of this product may increase dryness or irritation of the skin.

• If this occurs, only one medication should be used unless directed by a doctor.

Keep out of reach of children. If swallowed, get medical help or contact a Poison Control Center right away.

Directions

• Cleanse the skin thoroughly before applying medication.

• Cover the entire affected area with a thin layer 1 to 3 times daily.

• Because excessive drying of the skin may occur, start with one application daily, then gradually increase to two to three times daily if needed or as directed by a doctor.

• If bothersome dryness occurs, reduce application to once a day or every other day.

Inactive Ingredients

Silybum Marianum (Milk Thistle) Seed Oil, Nigella Sativa (Black Cumin) Seed Oil, Cucumis Sativus (Cucumber) Seed Oil, Punica Granatum (Pomegranate) Seed Oil, Diisopropyl Sebacate, Vaccinium Macrocarpon (Cranberry) Seed Oil, Dimethyl Isosorbide, Linum Usitatissimum (Flax) Seed Oil, Caprylic/Capric Triglyceride, Glycyrrhiza Glabra (Licorice) Root Extract, Prunus Armeniaca (Apricot) Kernel Oil, Hexylresorcinol, Ethyl Linoleate, Melia Azadirachta Leaf Extract, Chamomilla Recutita (Matricaria) Flower Oil, Citrus Aurantium Amara (Bitter Orange) Flower Oil, Melia Azadirachta Flower Extract, Helianthus Annuus (Sunflower) Seed Oil, 4-Terpineol, Simmondsia Chinensis (Jojoba) Seed Oil, Coccinia Indica Fruit Extract, Solanum Melongena (Eggplant) Fruit Extract, Amber Powder, Curcuma Longa (Turmeric) Root Extract, Curcuma Longa (Turmeric) Leaf Extract, Ocimum Sanctum Leaf Extract, Aloe Barbadensis Flower Extract, Corallina Officinalis Extract, Rosmarinus Officinalis (Rosemary) Leaf Extract, Moringa Oleifera Seed Oil, Tocopherol, Citrus Paradisi (Grapefruit) Peel Oil, Ocimum Basilicum (Basil) Flower/Leaf Extract.

for oily to acne-prone skin

ultra-clarifying

For the treatment and prevention of acne and blackheads, this 1.5% Salicylic Acid medicated, dry oil clears congested pores for smoother, blemish-free skin.

We are committed to producing transformative skincare that is kind to the planet.

B CORP CERTIFIED

We are B Corp certified, which means we meet the highest standards of verified social and environmental performance, public transparency, and legal accountability to balance profit and purpose.

CRUELTY-FREE

We are certified Cruelty-Free by both Leaping Bunny and PETA.

SUSTAINABLE

ENERGY EFFICIENT

We offset our carbon footprint for a cleaner, greener planet.

With 1.5% Salicylic Acid, this fast-acting, medicated treatment oil clears acne and blackhead-causing buildup and debris from congested pores for smoother, blemish-free skin.

Tea tree oil and black cumin seed oil support clear skin, while hexylresorcinol and licorice naturally brighten the appearance of old acne discolorations, for a visibly more even-toned complexion. Non-greasy milk thistle and cucumber seed oils prevent salicylic acid from over-drying the skin, while smoothing the appearance of lines and wrinkles. Chamomile and neroli soothe stressed, blemish-prone skin.

TO USE: Can be applied day or night. After cleansing skin, massage in U.F.O. to skin, neck, and chest, as needed. U.F.O. is a dry oil and will absorb quickly. Can also be applied to congested areas on the body.

PRO TIPS: If you are new to using salicylic acid, start by using U.F.O. 3x/week and work your way up to daily use. You can also mix 1-2 drops of U.F.O. into your foundation, before application, giving acne-fighting power to your makeup routine.

Made in USA of responsibly sourced domestic and foreign ingredients.
Dist: Sunday Riley Modern Skincare, LLC, Houston, TX 77027, USA.
EU RP: Obelis s.a., 1030 Brussels, BE. UK RP: Obelis UK Ltd.
Sandford Gate, Oxford, OX4 6LB. UK.
www.sundayriley.com